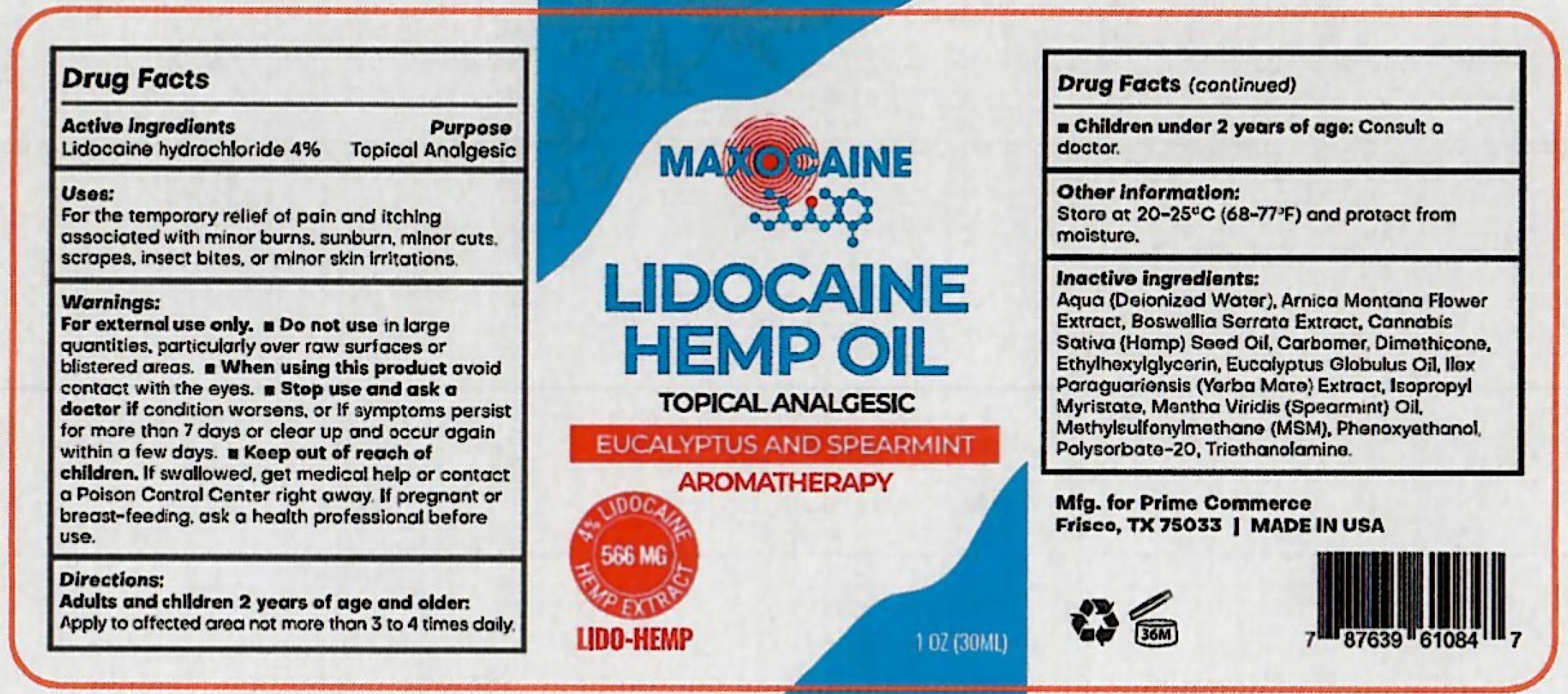 DRUG LABEL: MAXOCAINE Lidocaine Hemp Oil Topical Analgesic
NDC: 72188-188 | Form: SOLUTION
Manufacturer: Prime Commerce, LLC
Category: otc | Type: HUMAN OTC DRUG LABEL
Date: 20231111

ACTIVE INGREDIENTS: LIDOCAINE HYDROCHLORIDE 40 mg/1 mL
INACTIVE INGREDIENTS: WATER; ARNICA MONTANA FLOWER; INDIAN FRANKINCENSE; CANNABIS SATIVA SEED OIL; CARBOMER HOMOPOLYMER, UNSPECIFIED TYPE; DIMETHICONE; ETHYLHEXYLGLYCERIN; EUCALYPTUS OIL; ILEX PARAGUARIENSIS LEAF; ISOPROPYL MYRISTATE; SPEARMINT; DIMETHYL SULFONE; PHENOXYETHANOL; POLYSORBATE 20; TROLAMINE

MAXOCAINE Lidocaine Hemp Oil Topical Analgesic

Active Ingredients

Lidocaine hydrochloride 4%

Purpose

Topical Analgesic

Uses:

For the temporary relief of pain and itching associated with minor burns, sunburns, minor cuts, scrapes, insect bites, or minor skin irritations.

Warnings:

For external use only.

Do not use

- in large quantities. particularly over raw surfaces or blistered areas.

When using this product

- avoid contact with the eyes.

Stop use and ask a doctor if

- condition worsens, or if symptoms persist for more than 7 days or clear up and occur again within a few days.

Keep out of reach of children.

- If swallowed, get medical help or contact a Poison Control Center right away.

If pregnant or breast-feeding.

ask a health professional before use.

Directions:

- Apply to affected area not more than 3 to 4 times daily. Adults and children 2 years of age and older:
- Consult a doctor. Children under 2 year of age:

Other Information:

Store at 20-25°C (68-77°F) and protect from moisture.

Inactive ingredients

Aqua (Deionized Water), Arnica Montana Flower Extract, Boswellia Serrata Extract, Cannabis Sativa (Hemp) Seed Oil, Carbomer, Dimethicone, Ethylhexylglycerin, Eucalyptus Globulus Oil, Ilex Paraguariensis (Yerba Mate) Extract, Isopropyl Myristate, Mentha Viridis (Spearmint) Oil, Methylsulfonylmethane (MSM), Phenoxyethanol, Polysorbate-20, Triethanolamine.